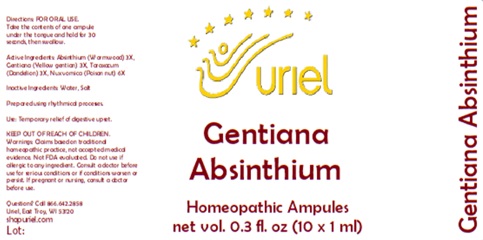 DRUG LABEL: Gentiana Absinthium
NDC: 48951-5007 | Form: LIQUID
Manufacturer: Uriel Pharmacy Inc.
Category: homeopathic | Type: HUMAN OTC DRUG LABEL
Date: 20250107

ACTIVE INGREDIENTS: WORMWOOD 3 [hp_X]/1 mL; GENTIANA LUTEA ROOT 3 [hp_X]/1 mL; TARAXACUM PALUSTRE ROOT 3 [hp_X]/1 mL; STRYCHNOS NUX-VOMICA SEED 6 [hp_X]/1 mL
INACTIVE INGREDIENTS: WATER; SODIUM CHLORIDE

Gentiana Absinthium

INDICATIONS AND USAGE

Directions: FOR ORAL USE.

DOSAGE AND ADMINISTRATION

Take the contents of one ampule under the tongue and hold for 30 seconds, then swallow.

ACTIVE INGREDIENT

Active Ingredients: Absinthium (Wormwood) 3X, Gentiana (Yellow gentian) 3X, Taraxacum (Dandelion) 3X, Nux vomica (Poison nut) 6X

Inactive Ingredients: Water, Salt

Prepared using rhythmical processes.

PURPOSE

Use: Temporary relief of digestive upset.

KEEP OUT OF REACH OF CHILDREN.

WARNINGS

Warnings: Claims based on traditional homeopathic practice, not accepted medical evidence. Not FDA evaluated. Do not use if allergic to any ingredient. Consult a doctor before use for serious conditions or if conditions worsen or persist. If pregnant or nursing, consult a doctor before use.

Questions? Call 866.642.2858
Uriel, East Troy, WI 53120
shopuriel.com

Lot: